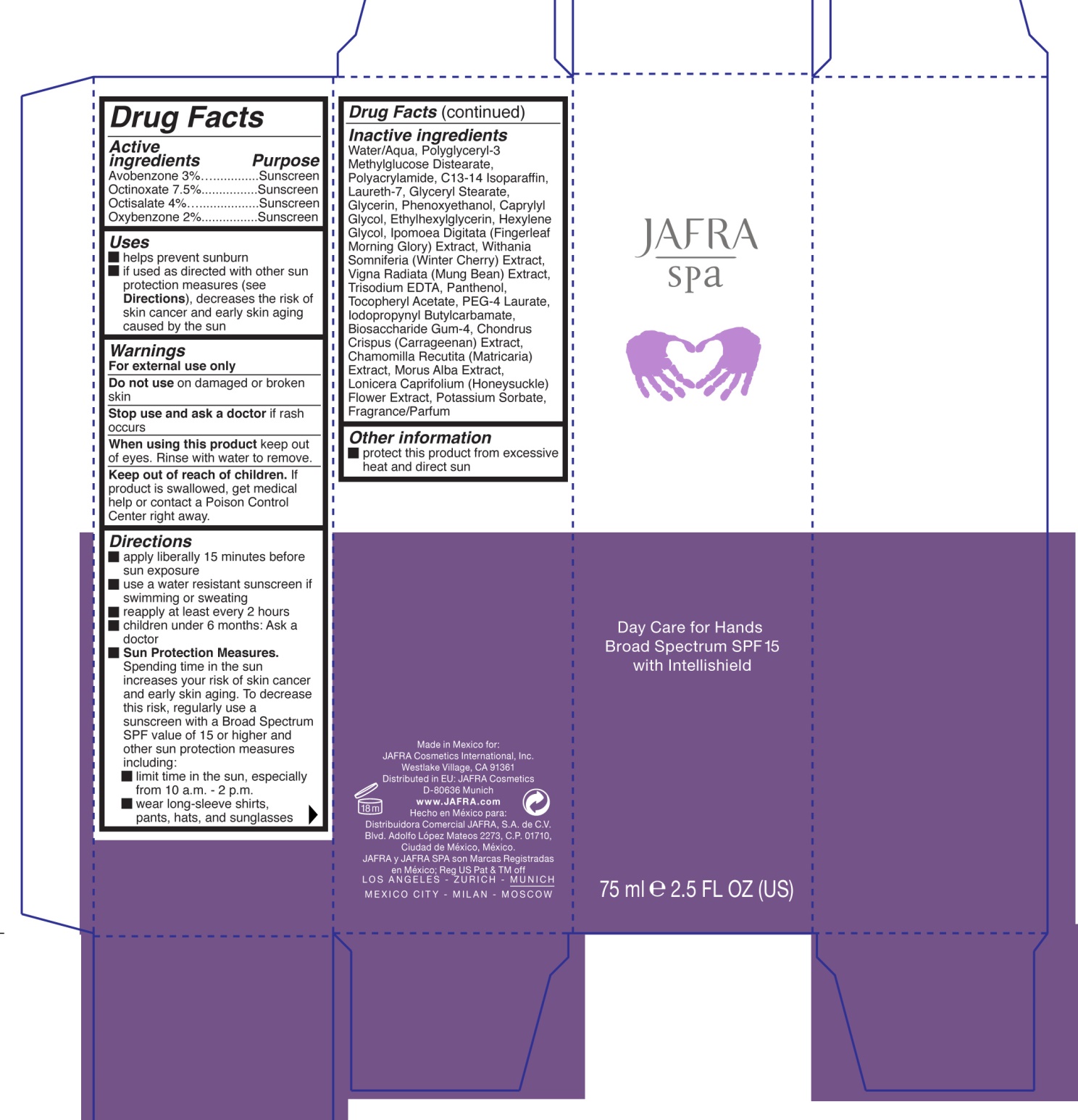 DRUG LABEL: Day Care for Hands Broad Spectrum SPF 15
NDC: 68828-400 | Form: CREAM
Manufacturer: JAFRA COSMETICS INTERNATIONAL
Category: otc | Type: HUMAN OTC DRUG LABEL
Date: 20181205

ACTIVE INGREDIENTS: AVOBENZONE 3 g/75 mL; OCTINOXATE 7.5 g/75 mL; OCTISALATE 4 g/75 mL; OXYBENZONE 2 g/75 mL
INACTIVE INGREDIENTS: WATER; POLYACRYLAMIDE (1500 MW); C13-14 ISOPARAFFIN; LAURETH-7; GLYCERYL MONOSTEARATE; GLYCERIN; PHENOXYETHANOL; CAPRYLYL GLYCOL; ETHYLHEXYLGLYCERIN; HEXYLENE GLYCOL; EDETATE TRISODIUM; PANTHENOL; .ALPHA.-TOCOPHEROL ACETATE; PEG-4 LAURATE; IODOPROPYNYL BUTYLCARBAMATE; BIOSACCHARIDE GUM-4; CHONDRUS CRISPUS CARRAGEENAN; MATRICARIA RECUTITA; LONICERA CAPRIFOLIUM FLOWER; POTASSIUM SORBATE

JAFRA - Day Care for Hands SPF 15

Active Ingredients Purpose

Avobenzone 3% ......................... Sunscreen

Octinoxate 7.5% ......................... Sunscreen

Octisalate 4% ............................. Sunscreen

Oxybenzone 2% ......................... Sunscreen

Uses

- Helps prevent sunburn
- If used as directed with other sun protection measures (see Directions), decreases the risk of skin cancer and early skin aging caused by the sun

Keep out of reach of children. If product is swallowed, get medical help or contact a Poison Control Center right away.

Stop use and ask a doctor if rash occurs

Warnings

- For external use only
- Do not use on damaged or broken skin
- When using this product keep out of eyes. Rinse with water to remove.

Directions

- apply liberally 15 minutes before sun exposure
- use a water resistant sunscreen if swimming or sweating
- reapply at least every 2 hours
- children under 6 minths: Ask a doctor
- Sun Protection Measures. Spending time in the sun increases your risk of skin cancer and early skin aging. To decrease this risk, regularly use a sunscreen with a Broad Spectrum SPF value of 15 or higher and other sun protection measures including:
- limit time in the sun, especially from 10a.m. - 2p.m.
- wear long-sleeve shirts, pants, hats, and sunglasses

INACTIVE INGREDIENT

Water/Aqua, Polyglycery-3 Methylglucose Distearate, Polyacrylamide, C13-14 Isoparaffin, Laureth-7, Glyceryl Stearate, Glycerin, Phenoxyethanol, Caprylyl Glycol, Ethylhexylglycerin, Hexylene Glycol, Ipomoea Digitata (Fingerleaf Morning Glory) Extract, Withania Somniferia (Winter Cherry) Extract, Vigna Radiata (Mung Bean) Extract, Trisodium EDTA, Panthenol, Tocopheryl Acetate, PEG-4 Laurate, Iodopropynyl Butylcarbamate, Biasacchardie Gum-4, Chondrus Crispus (Carrageenan) Extract, Chamomilla Recutita (Matricaria) Extact, Morus Alba Extract, Lonicera Caprifolium (Honeysuckle) Flower Extract, Potassium Sorbate, Fragrance/Parfum

PACKAGE LABEL

JAFRA

spa

Day Care for Hands

Broad Spectrum SPF 15

with intellishield

75ml e 2.5 FL OZ (US)